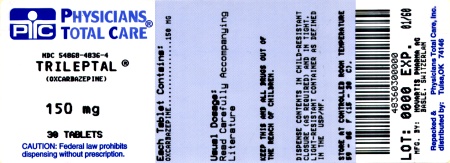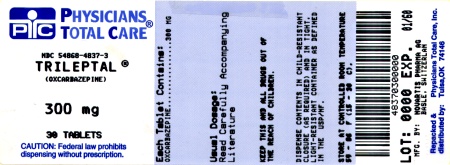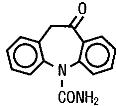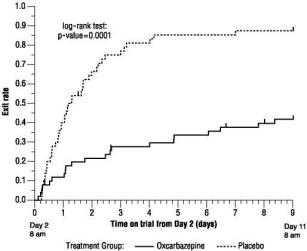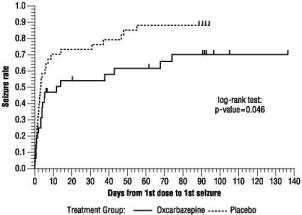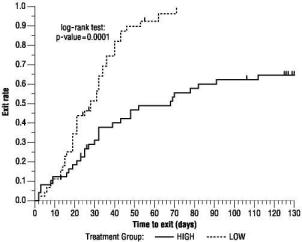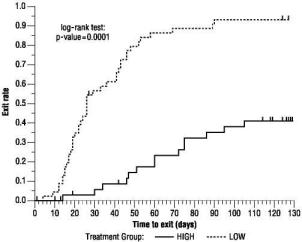 DRUG LABEL: Trileptal
NDC: 54868-4836 | Form: TABLET, FILM COATED
Manufacturer: Physicians Total Care, Inc.
Category: prescription | Type: HUMAN PRESCRIPTION DRUG LABEL
Date: 20120217

ACTIVE INGREDIENTS: OXCARBAZEPINE 150 mg/1 1
INACTIVE INGREDIENTS: SILICON DIOXIDE; CROSPOVIDONE; HYPROMELLOSES; FERRIC OXIDE YELLOW; MAGNESIUM STEARATE; CELLULOSE, MICROCRYSTALLINE; POLYETHYLENE GLYCOL; TALC; TITANIUM DIOXIDE

HIGHLIGHTS OF PRESCRIBING INFORMATION

These highlights do not include all the information needed to use Trileptal safely and effectively. See full prescribing information for Trileptal.
Trileptal® (oxcarbazepine) film-coated tablets
Trileptal® (oxcarbazepine) oral suspension for oral administration
Initial U.S. Approval: 2000

1 INDICATIONS AND USAGE

Trileptal is an antiepileptic drug indicated for:

- Adults:
  - Monotherapy or adjunctive therapy in the treatment of partial seizures
- Children:
  - Monotherapy in the treatment of partial seizures in children 4-16 years
  - Adjunctive therapy in the treatment of partial seizures in children 2-16 years (1)

2 DOSAGE AND ADMINISTRATION

ADULTS: initiated with a dose of 600 mg/day, given in twice-a-day regimen

- Adjunctive Therapy: Maximum increment of 600 mg/day at approximately weekly intervals. The recommended daily dose is 1200 mg/day (2.1)
- Conversion to Monotherapy: Concomitant AEDs should be completely withdrawn over 3-6 weeks, while maximum dose of Trileptal should be reached in about 2-4 weeks. Maximum increment of 600 mg/day at approximately weekly intervals to a recommended daily dose of 2400 mg/day (2.2)
- Initiation of Monotherapy: Increments of 300 mg/day every third day to a dose of 1200 mg/day. (2.3)

CHILDREN: initiation with 8-10 mg/kg/day, given in twice-a-day regimen. For patients aged 2 - <4 years and under 20 kg, a starting dose of 16 to 20 mg/kg/day may be considered. Recommended daily dose is dependent upon patient weight

- Adjunctive Patients (Aged 2-16 Years): For patients aged 4-16 years, target maintenance dose should be achieved over 2 weeks (2.4). For patients aged 2 - <4 years, maximum maintenance dose should be achieved over 2-4 weeks and should not to exceed 60mg/kg/day (2.4)
- Conversion to Monotherapy for Patients (Aged 4-16 Years)
  Maximum increment of 10 mg/kg/day at weekly intervals, concomitant antiepileptic drugs can be completely withdrawn over 3-6 weeks (2.5)
- Initiation of Monotherapy for Patients (Aged 4-16 Years)
  Increments of 5 mg/kg/day every third day (2.6)

3 DOSAGE FORMS AND STRENGTHS

- Film-coated tablets: 150 mg, 300 mg and 600 mg (3)
- Oral suspension a 300 mg/5 mL (60 mg/mL) (3)

4 CONTRAINDICATIONS

- Trileptal should not be used in patients with a known hypersensitivity to oxcarbazepine or to any of its components (4)

5 WARNINGS AND PRECAUTIONS

- Hyponatremia (5.1)
- Anaphylactic Reactions and Angioedema (5.2)
- Patients with a Past History of Hypersensitivity Reaction to Carbamazepine (5.3)
- Serious Dermatological Reactions (5.4)
- Suicidal Behavior and Ideation (5.5)
- Withdrawal of AEDs (5.6)
- Cognitive/Neuropsychiatric Adverse Events (5.7)
- Multi-Organ Hypersensitivity (5.8)
- Hematologic Events (5.9)
- Seizure Control During Pregnancy (5.10)
- Laboratory Tests (5.11)

6 ADVERSE REACTIONS

The most commonly observed (≥5%) adverse experiences were: dizziness, somnolence, diplopia, fatigue, nausea, vomiting, ataxia, abnormal vision, abdominal pain, tremor, dyspepsia, abnormal gait, and in pediatric patients <4 years old, also infections and infestations. (6.1)

To report SUSPECTED ADVERSE REACTIONS, contact Novartis Pharmaceuticals Corporation at 1-888-669-6682 or FDA at 1-800-FDA-1088 or www.fda.gov/medwatch.

7 DRUG INTERACTIONS

- Phenytoin: Increased phenytoin levels. Reduced dose of phenytoin may be required. (7.1)
- Carbamazepine: Decreased plasma levels of MHD (the active metabolite). Dose adjustments may be necessary. (7.1)
- Phenobarbital: Decreased plasma levels of MHD. Dose adjustments may be necessary. (7.1)
- Oral Contraceptive: Patients should be advised that Trileptal may decrease the effectiveness of hormonal contraceptives. (7.2)

8 USE IN SPECIFIC POPULATIONS

- Pregnancy: Plasma levels of MHD may be decreased. Monitor patients. Based on animal data, may cause fetal harm. To enroll in the North American Antiepileptic Drug Pregnancy Registry call (888) 233-2334 (toll free). (8.1)
- In patients with a creatinine clearance <30mL/min, Trileptal should be started at one-half the usual starting dose and increased slowly (2, 8.6, 12.3)

FULL PRESCRIBING INFORMATION

1 INDICATIONS AND USAGE

Trileptal is indicated for use as monotherapy or adjunctive therapy in the treatment of partial seizures in adults and as monotherapy in the treatment of partial seizures in children aged 4 years and above with epilepsy, and as adjunctive therapy in children aged 2 years and above with partial seizures.

2 DOSAGE AND ADMINISTRATION

All dosing should be given in a twice-a-day regimen. Trileptal oral suspension and Trileptal film-coated tablets may be interchanged at equal doses.

Trileptal should be kept out of the reach and sight of children.

Before using Trileptal oral suspension, shake the bottle well and prepare the dose immediately afterwards. The prescribed amount of oral suspension should be withdrawn from the bottle using the oral dosing syringe supplied. Trileptal oral suspension can be mixed in a small glass of water just prior to administration or, alternatively, may be swallowed directly from the syringe. After each use, close the bottle and rinse the syringe with warm water and allow it to dry thoroughly.

Trileptal can be taken with or without food [see Clinical Pharmacology (12.3)].

2.1 Adjunctive Therapy for Adults

Treatment with Trileptal should be initiated with a dose of 600 mg/day, given in a twice-a-day regimen. If clinically indicated, the dose may be increased by a maximum of 600 mg/day at approximately weekly intervals; the recommended daily dose is 1200 mg/day. Daily doses above 1200 mg/day show somewhat greater effectiveness in controlled trials, but most patients were not able to tolerate the 2400 mg/day dose, primarily because of CNS effects. It is recommended that the patient be observed closely and plasma levels of the concomitant AEDs be monitored during the period of Trileptal titration, as these plasma levels may be altered, especially at Trileptal doses greater than 1200 mg/day [see Drug Interactions (7.1)].

2.2 Conversion to Monotherapy for Adults

Patients receiving concomitant AEDs may be converted to monotherapy by initiating treatment with Trileptal at 600 mg/day (given in a twice-a-day regimen) while simultaneously initiating the reduction of the dose of the concomitant AEDs. The concomitant AEDs should be completely withdrawn over 3-6 weeks, while the maximum dose of Trileptal should be reached in about 2-4 weeks. Trileptal may be increased as clinically indicated by a maximum increment of 600 mg/day at approximately weekly intervals to achieve the recommended daily dose of 2400 mg/day. A daily dose of 1200 mg/day has been shown in one study to be effective in patients in whom monotherapy has been initiated with Trileptal. Patients should be observed closely during this transition phase.

2.3 Initiation of Monotherapy for Adults

Patients not currently being treated with AEDs may have monotherapy initiated with Trileptal. In these patients, Trileptal should be initiated at a dose of 600 mg/day (given in a twice-a-day regimen); the dose should be increased by 300 mg/day every third day to a dose of 1200 mg/day. Controlled trials in these patients examined the effectiveness of a 1200 mg/day dose; a dose of 2400 mg/day has been shown to be effective in patients converted from other AEDs to Trileptal monotherapy (see above).

2.4 Adjunctive Therapy for Pediatric Patients (Aged 2-16 Years)

In pediatric patients aged 4-16 years, treatment should be initiated at a daily dose of 8-10 mg/kg generally not to exceed 600 mg/day, given in a twice-a-day regimen. The target maintenance dose of Trileptal should be achieved over two weeks, and is dependent upon patient weight, according to the following chart:

20-29 kg - 900 mg/day

29.1-39 kg - 1200 mg/day

>39 kg - 1800 mg/day

In the clinical trial, in which the intention was to reach these target doses, the median daily dose was 31 mg/kg with a range of 6-51 mg/kg.

In pediatric patients aged 2-<4 years, treatment should also be initiated at a daily dose of 8-10 mg/kg generally not to exceed 600 mg/day, given in a twice-a-day regimen. For patients under 20 kg, a starting dose of 16-20 mg/kg may be considered [see Clinical Pharmacology (12.3)]. The maximum maintenance dose of Trileptal should be achieved over 2-4 weeks and should not exceed 60 mg/kg/day in a twice-a-day regimen.

In the clinical trial in pediatric patients (2 to 4 years of age) in which the intention was to reach the target dose of 60 mg/kg/day, 50% of patients reached a final dose of at least 55 mg/kg/day.

Under adjunctive therapy (with and without enzyme-inducing AEDs), when normalized by body weight, apparent clearance (L/hr/kg) decreased when age increased such that children 2 to <4 years of age may require up to twice the oxcarbazepine dose per body weight compared to adults; and children 4 to ≤12 years of age may require a 50% higher oxcarbazepine dose per body weight compared to adults.

2.5 Conversion to Monotherapy for Pediatric Patients (Aged 4-16 Years)

Patients receiving concomitant antiepileptic drugs may be converted to monotherapy by initiating treatment with Trileptal at approximately 8-10 mg/kg/day given in a twice-a-day regimen, while simultaneously initiating the reduction of the dose of the concomitant antiepileptic drugs. The concomitant antiepileptic drugs can be completely withdrawn over 3-6 weeks while Trileptal may be increased as clinically indicated by a maximum increment of 10 mg/kg/day at approximately weekly intervals to achieve the recommended daily dose. Patients should be observed closely during this transition phase.

The recommended total daily dose of Trileptal is shown in the table below.

2.6 Initiation of Monotherapy for Pediatric Patients (Aged 4-16 Years)

Patients not currently being treated with antiepileptic drugs may have monotherapy initiated with Trileptal. In these patients, Trileptal should be initiated at a dose of 8-10 mg/kg/day given in a twice-a-day regimen. The dose should be increased by 5 mg/kg/day every third day to the recommended daily dose shown in the table below.

Table 1 Range of Maintenance Doses of Trileptal for Children by Weight During Monotherapy
 | From | To
Weight in kg | Dose (mg/day) | Dose (mg/day)
20 | 600 | 900
25 | 900 | 1200
30 | 900 | 1200
35 | 900 | 1500
40 | 900 | 1500
45 | 1200 | 1500
50 | 1200 | 1800
55 | 1200 | 1800
60 | 1200 | 2100
65 | 1200 | 2100
70 | 1500 | 2100

2.7 Patients with Hepatic Impairment

In general, dose adjustments are not required in patients with mild-to-moderate hepatic impairment [see Clinical Pharmacology (12.3).]

2.8 Patients with Renal Impairment

In patients with impaired renal function (creatinine clearance <30 mL/min) Trileptal therapy should be initiated at one-half the usual starting dose (300 mg/day) and increased slowly to achieve the desired clinical response [see Clinical Pharmacology (12.3)]

3 DOSAGE FORMS AND STRENGTHS

Film-coated Tablets: 150 mg, 300 mg and 600 mg. Oral Suspension: 300 mg/5 mL (60 mg/mL)

4 CONTRAINDICATIONS

Trileptal should not be used in patients with a known hypersensitivity to oxcarbazepine or to any of its components.

5 WARNINGS AND PRECAUTIONS

5.1 Hyponatremia

Clinically significant hyponatremia (sodium <125 mmol/L) can develop during Trileptal use. In the 14 controlled epilepsy studies 2.5% of Trileptal-treated patients (38/1,524) had a sodium of less than 125 mmol/L at some point during treatment, compared to no such patients assigned placebo or active control (carbamazepine and phenobarbital for adjunctive and monotherapy substitution studies, and phenytoin and valproate for the monotherapy initiation studies). Clinically significant hyponatremia generally occurred during the first three months of treatment with Trileptal, although there were patients who first developed a serum sodium <125 mmol/L more than one year after initiation of therapy. Most patients who developed hyponatremia were asymptomatic but patients in the clinical trials were frequently monitored and some had their Trileptal dose reduced, discontinued, or had their fluid intake restricted for hyponatremia. Whether or not these maneuvers prevented the occurrence of more severe events is unknown. Cases of symptomatic hyponatremia have been reported during post-marketing use. In clinical trials, patients whose treatment with Trileptal was discontinued due to hyponatremia generally experienced normalization of serum sodium within a few days without additional treatment.

Measurement of serum sodium levels should be considered for patients during maintenance treatment with Trileptal, particularly if the patient is receiving other medications known to decrease serum sodium levels (for example, drugs associated with inappropriate ADH secretion) or if symptoms possibly indicating hyponatremia develop (e.g., nausea, malaise, headache, lethargy, confusion, obtundation, or increase in seizure frequency or severity).

5.2 Anaphylactic Reactions and Angioedema

Rare cases of anaphylaxis and angioedema involving the larynx, glottis, lips and eyelids have been reported in patients after taking the first or subsequent doses of Trileptal. Angioedema associated with laryngeal edema can be fatal. If a patient develops any of these reactions after treatment with Trileptal, the drug should be discontinued and an alternative treatment started. These patients should not be rechallenged with the drug [see Warnings and Precautions (5.3)].

5.3 Patients with a Past History of Hypersensitivity Reaction to Carbamazepine

Patients who have had hypersensitivity reactions to carbamazepine should be informed that approximately 25%-30% of them will experience hypersensitivity reactions with Trileptal. For this reason patients should be specifically questioned about any prior experience with carbamazepine, and patients with a history of hypersensitivity reactions to carbamazepine should ordinarily be treated with Trileptal only if the potential benefit justifies the potential risk. If signs or symptoms of hypersensitivity develop, Trileptal should be discontinued immediately [see Warnings and Precautions (5.2, 5.8)].

5.4 Serious Dermatological Reactions

Serious dermatological reactions, including Stevens-Johnson syndrome (SJS) and toxic epidermal necrolysis (TEN), have been reported in both children and adults in association with Trileptal use. The median time of onset for reported cases was 19 days. Such serious skin reactions may be life threatening, and some patients have required hospitalization with very rare reports of fatal outcome. Recurrence of the serious skin reactions following rechallenge with Trileptal has also been reported.

The reporting rate of TEN and SJS associated with Trileptal use, which is generally accepted to be an underestimate due to underreporting, exceeds the background incidence rate estimates by a factor of 3- to 10-fold. Estimates of the background incidence rate for these serious skin reactions in the general population range between 0.5 to 6 cases per million-person years. Therefore, if a patient develops a skin reaction while taking Trileptal, consideration should be given to discontinuing Trileptal use and prescribing another antiepileptic medication.

5.5 Suicidal Behavior and Ideation

Antiepileptic drugs (AEDs), including Trileptal, increase the risk of suicidal thoughts or behavior in patients taking these drugs for any indication. Patients treated with any AED for any indication should be monitored for the emergence or worsening of depression, suicidal thoughts or behavior, and/or any unusual changes in mood or behavior.

Pooled analyses of 199 placebo-controlled clinical trials (mono- and adjunctive therapy) of 11 different AEDs showed that patients randomized to one of the AEDs had approximately twice the risk (adjusted Relative Risk 1.8, 95% CI:1.2, 2.7) of suicidal thinking or behavior compared to patients randomized to placebo. In these trials, which had a median treatment duration of 12 weeks, the estimated incidence rate of suicidal behavior or ideation among 27,863 AED-treated patients was 0.43%, compared to 0.24% among 16,029 placebo-treated patients, representing an increase of approximately one case of suicidal thinking or behavior for every 530 patients treated. There were four suicides in drug-treated patients in the trials and none in placebo-treated patients, but the number is too small to allow any conclusion about drug effect on suicide.

The increased risk of suicidal thoughts or behavior with AEDs was observed as early as one week after starting drug treatment with AEDs and persisted for the duration of treatment assessed. Because most trials included in the analysis did not extend beyond 24 weeks, the risk of suicidal thoughts or behavior beyond 24 weeks could not be assessed.

The risk of suicidal thoughts or behavior was generally consistent among drugs in the data analyzed. The finding of increased risk with AEDs of varying mechanisms of action and across a range of indications suggests that the risk applies to all AEDs used for any indication. The risk did not vary substantially by age (5-100 years) in the clinical trials analyzed. Table 2 shows absolute and relative risk by indication for all evaluated AEDs.

Table 2 Risk by Indication for Antiepileptic Drugs in the Pooled Analysis
Indication | Placebo Patients with Events Per 1,000 Patients | Drug Patients with Events Per 1,000 Patients | Relative Risk: Incidence of Events in Drug Patients/Incidence in Placebo Patients | Risk Difference: Additional Drug Patients with Events Per 1,000 Patients
Epilepsy | 1.0 | 3.4 | 3.5 | 2.4
Psychiatric | 5.7 | 8.5 | 1.5 | 2.9
Other | 1.0 | 1.8 | 1.9 | 0.9
Total | 2.4 | 4.3 | 1.8 | 1.9

The relative risk for suicidal thoughts or behavior was higher in clinical trials for epilepsy than in clinical trials for psychiatric or other conditions, but the absolute risk differences were similar for the epilepsy and psychiatric indications.

Anyone considering prescribing Trileptal or any other AED must balance the risk of suicidal thoughts or behavior with the risk of untreated illness. Epilepsy and many other illnesses for which AEDs are prescribed are themselves associated with morbidity and mortality and an increased risk of suicidal thoughts and behavior. Should suicidal thoughts and behavior emerge during treatment, the prescriber needs to consider whether the emergence of these symptoms in any given patient may be related to the illness being treated.

Patients, their caregivers, and families should be informed that AEDs increase the risk of suicidal thoughts and behavior and should be advised of the need to be alert for the emergence or worsening of the signs and symptoms of depression, any unusual changes in mood or behavior, or the emergence of suicidal thoughts, behavior, or thoughts about self-harm. Behaviors of concern should be reported immediately to healthcare providers.

5.6 Withdrawal of AEDs

As with all antiepileptic drugs, Trileptal should be withdrawn gradually to minimize the potential of increased seizure frequency.

5.7 Cognitive/Neuropsychiatric Adverse Events

Use of Trileptal has been associated with central nervous system-related adverse events. The most significant of these can be classified into three general categories: 1) cognitive symptoms including psychomotor slowing, difficulty with concentration, and speech or language problems, 2) somnolence or fatigue, and 3) coordination abnormalities, including ataxia and gait disturbances.

Adult Patients

In one large, fixed-dose study, Trileptal was added to existing AED therapy (up to three concomitant AEDs). By protocol, the dosage of the concomitant AEDs could not be reduced as Trileptal was added, reduction in Trileptal dosage was not allowed if intolerance developed, and patients were discontinued if unable to tolerate their highest target maintenance doses. In this trial, 65% of patients were discontinued because they could not tolerate the 2400 mg/day dose of Trileptal on top of existing AEDs. The adverse events seen in this study were primarily CNS related and the risk for discontinuation was dose related.

In this trial, 7.1% of oxcarbazepine-treated patients and 4% of placebo-treated patients experienced a cognitive adverse event. The risk of discontinuation for these events was about 6.5 times greater on oxcarbazepine than on placebo. In addition, 26% of oxcarbazepine-treated patients and 12% of placebo-treated patients experienced somnolence. The risk of discontinuation for somnolence was about 10 times greater on oxcarbazepine than on placebo. Finally, 28.7% of oxcarbazepine-treated patients and 6.4% of placebo-treated patients experienced ataxia or gait disturbances. The risk for discontinuation for these events was about seven times greater on oxcarbazepine than on placebo.

In a single placebo-controlled monotherapy trial evaluating 2400 mg/day of Trileptal, no patients in either treatment group discontinued double-blind treatment because of cognitive adverse events, somnolence, ataxia, or gait disturbance.

In the two dose-controlled conversion to monotherapy trials comparing 2400 mg/day and 300 mg/day Trileptal, 1.1% of patients in the 2400 mg/day group discontinued double-blind treatment because of somnolence or cognitive adverse events compared to 0% in the 300 mg/day group. In these trials, no patients discontinued because of ataxia or gait disturbances in either treatment group.

Pediatric Patients

A study was conducted in pediatric patients (3 to 17 years old) with inadequately controlled partial seizures in which Trileptal was added to existing AED therapy (up to two concomitant AEDs). By protocol, the dosage of concomitant AEDs could not be reduced as Trileptal was added. Trileptal was titrated to reach a target dose ranging from 30 mg/kg to 46 mg/kg (based on a patient’s body weight with fixed doses for predefined weight ranges).

Cognitive adverse events occurred in 5.8% of oxcarbazepine-treated patients (the single most common event being concentration impairment, 4 of 138 patients) and in 3.1% of patients treated with placebo. In addition, 34.8% of oxcarbazepine-treated patients and 14.0% of placebo-treated patients experienced somnolence. (No patient discontinued due to a cognitive adverse event or somnolence.). Finally, 23.2% of oxcarbazepine-treated patients and 7.0% of placebo-treated patients experienced ataxia or gait disturbances. Two (1.4%) oxcarbazepine-treated patients and 1 (0.8%) placebo-treated patient discontinued due to ataxia or gait disturbances.

5.8 Multi-Organ Hypersensitivity

Multi-organ hypersensitivity reactions have occurred in close temporal association (median time to detection 13 days: range 4-60) to the initiation of Trileptal therapy in adult and pediatric patients. Although there have been a limited number of reports, many of these cases resulted in hospitalization and some were considered life threatening. Signs and symptoms of this disorder were diverse; however, patients typically, although not exclusively, presented with fever and rash associated with other organ system involvement. These may include hematologic and lymphatic (e.g., eosinophilia, thrombocytopenia, lymphadenopathy, leukopenia, neutropenia, splenomegaly), hepatobiliary (e.g., hepatitis, liver function test abnormalities), renal (e.g., proteinuria, nephritis, oliguria, renal failure), muscles and joints (e.g., joint swelling, myalgia, arthralgia, asthenia), nervous system (e.g., hepatic encephalopathy), respiratory (e.g., dyspnea, pulmonary edema, asthma, bronchospasm, interstitial lung disease), hepatorenal syndrome, pruritus, and angioedema. Because the disorder is variable in its expression, other organ system symptoms and signs, not noted here, may occur. If this reaction is suspected, Trileptal should be discontinued and an alternative treatment started. Although there are no case reports to indicate cross sensitivity with other drugs that produce this syndrome, the experience amongst drugs associated with multi-organ hypersensitivity would indicate this to be a possibility [see Warnings and Precautions (5.3)].

5.9 Hematologic Events

Rare reports of pancytopenia, agranulocytosis, and leukopenia have been seen in patients treated with Trileptal during post-marketing experience. Discontinuation of the drug should be considered if any evidence of these hematologic events develop.

5.10 Seizure Control During Pregnancy

Due to physiological changes during pregnancy, plasma levels of the active metabolite of oxcarbazepine, the 10-monohydroxy derivative (MHD), may gradually decrease throughout pregnancy. It is recommended that patients be monitored carefully during pregnancy. Close monitoring should continue through the postpartum period because MHD levels may return after delivery.

5.11 Laboratory Tests

Serum sodium levels below 125 mmol/L have been observed in patients treated with Trileptal [see Warnings and Precautions (5.1)]. Experience from clinical trials indicates that serum sodium levels return toward normal when the Trileptal dosage is reduced or discontinued, or when the patient was treated conservatively (e.g., fluid restriction).

Laboratory data from clinical trials suggest that Trileptal use was associated with decreases in T4, without changes in T3 or TSH.

6 ADVERSE REACTIONS

Because clinical trials are conducted under widely varying conditions, adverse reaction rates observed in the clinical trials of a drug cannot be directly compared to rates in the clinical trials of another drug and may not reflect the rates observed in practice.

6.1 Clinical Studies Experience

Most Common Adverse Reactions in All Clinical Studies

Adjunctive Therapy/Monotherapy in Adults Previously Treated with other AEDs: The most commonly observed (≥5%) adverse reactions seen in association with Trileptal and substantially more frequent than in placebo-treated patients were: dizziness, somnolence, diplopia, fatigue, nausea, vomiting, ataxia, abnormal vision, abdominal pain, tremor, dyspepsia, abnormal gait.

Approximately 23% of these 1,537 adult patients discontinued treatment because of an adverse experience. The adverse reactions most commonly associated with discontinuation were: dizziness (6.4%), diplopia (5.9%), ataxia (5.2%), vomiting (5.1%), nausea (4.9%), somnolence (3.8%), headache (2.9%), fatigue (2.1%), abnormal vision (2.1%), tremor (1.8%), abnormal gait (1.7%), rash (1.4%), hyponatremia (1.0%).

Monotherapy in Adults Not Previously Treated with other AEDs: The most commonly observed (≥5%) adverse reactions seen in association with Trileptal in these patients were similar to those in previously treated patients.

Approximately 9% of these 295 adult patients discontinued treatment because of an adverse experience. The adverse reactions most commonly associated with discontinuation were: dizziness (1.7%), nausea (1.7%), rash (1.7%), headache (1.4%).

Adjunctive Therapy/Monotherapy in Pediatric Patients 4 Years Old and Above Previously Treated with other AEDs: The most commonly observed (≥5%) adverse reactions seen in association with Trileptal in these patients were similar to those seen in adults.

Approximately 11% of these 456 pediatric patients discontinued treatment because of an adverse experience. The adverse reactions most commonly associated with discontinuation were: somnolence (2.4%), vomiting (2.0%), ataxia (1.8%), diplopia (1.3%), dizziness (1.3%), fatigue (1.1%), nystagmus (1.1%).

Monotherapy in Pediatric Patients 4 Years Old and Above Not Previously Treated with other AEDs: The most commonly observed (≥5%) adverse reactions seen in association with Trileptal in these patients were similar to those in adults.

Approximately 9.2% of 152 pediatric patients discontinued treatment because of an adverse experience. The adverse reactions most commonly associated (≥1%) with discontinuation were rash (5.3%) and maculopapular rash (1.3%).

Adjunctive Therapy/Monotherapy in Pediatric Patients 1 Month to <4 Years Old Previously Treated or Not Previously Treated with other AEDs: The most commonly observed (≥5%) adverse reactions seen in association with Trileptal in these patients were similar to those seen in older children and adults except for infections and infestations which were more frequently seen in these younger children.

Approximately 11% of these 241 pediatric patients discontinued treatment because of an adverse experience. The adverse reaction most commonly associated with discontinuation were: convulsions (3.7%), status epilepticus (1.2%), and ataxia (1.2%).

Incidence in Controlled Clinical Studies: The prescriber should be aware that the figures in Tables 3, 4, 5 and 6 cannot be used to predict the frequency of adverse reactions in the course of usual medical practice where patient characteristics and other factors may differ from those prevailing during clinical studies. Similarly, the cited frequencies cannot be directly compared with figures obtained from other clinical investigations involving different treatments, uses, or investigators. An inspection of these frequencies, however, does provide the prescriber with one basis to estimate the relative contribution of drug and nondrug factors to the adverse event incidences in the population studied.

Controlled Clinical Studies of Adjunctive Therapy/Monotherapy in Adults Previously Treated with other AEDs: Table 3 lists treatment-emergent signs and symptoms that occurred in at least 2% of adult patients with epilepsy treated with Trileptal or placebo as adjunctive treatment and were numerically more common in the patients treated with any dose of Trileptal. Table 4 lists treatment-emergent signs and symptoms in patients converted from other AEDs to either high dose Trileptal or low dose (300 mg) Trileptal. Note that in some of these monotherapy studies patients who dropped out during a preliminary tolerability phase are not included in the tables.

Table 3 Treatment-Emergent Adverse Event Incidence in a Controlled Clinical Study of Adjunctive Therapy in Adults (Events in at Least 2% of Patients Treated with 2400 mg/day of Trileptal and Numerically More Frequent than in the Placebo Group)
 | Oxcarbazepine Dosage (mg/day)
Body System/ Adverse Event | OXC 600 N=163 % | OXC 1200 N=171 % | OXC 2400 N=126 % | Placebo N=166 %
Body as a Whole
Fatigue | 15 | 12 | 15 | 7
Asthenia | 6 | 3 | 6 | 5
Edema Legs | 2 | 1 | 2 | 1
Weight Increase | 1 | 2 | 2 | 1
Feeling Abnormal | 0 | 1 | 2 | 0
Cardiovascular System
Hypotension | 0 | 1 | 2 | 0
Digestive System
Nausea | 15 | 25 | 29 | 10
Vomiting | 13 | 25 | 36 | 5
Pain Abdominal | 10 | 13 | 11 | 5
Diarrhea | 5 | 6 | 7 | 6
Dyspepsia | 5 | 5 | 6 | 2
Constipation | 2 | 2 | 6 | 4
Gastritis | 2 | 1 | 2 | 1
Metabolic and Nutritional Disorders
Hyponatremia | 3 | 1 | 2 | 1
Musculoskeletal System
Muscle Weakness | 1 | 2 | 2 | 0
Sprains and Strains | 0 | 2 | 2 | 1
Nervous System
Headache | 32 | 28 | 26 | 23
Dizziness | 26 | 32 | 49 | 13
Somnolence | 20 | 28 | 36 | 12
Ataxia | 9 | 17 | 31 | 5
Nystagmus | 7 | 20 | 26 | 5
Gait Abnormal | 5 | 10 | 17 | 1
Insomnia | 4 | 2 | 3 | 1
Tremor | 3 | 8 | 16 | 5
Nervousness | 2 | 4 | 2 | 1
Agitation | 1 | 1 | 2 | 1
Coordination Abnormal | 1 | 3 | 2 | 1
EEG Abnormal | 0 | 0 | 2 | 0
Speech Disorder | 1 | 1 | 3 | 0
Confusion | 1 | 1 | 2 | 1
Cranial Injury NOS | 1 | 0 | 2 | 1
Dysmetria | 1 | 2 | 3 | 0
Thinking Abnormal | 0 | 2 | 4 | 0
Respiratory System
Rhinitis | 2 | 4 | 5 | 4
Skin and Appendages
Acne | 1 | 2 | 2 | 0
Special Senses
Diplopia | 14 | 30 | 40 | 5
Vertigo | 6 | 12 | 15 | 2
Vision Abnormal | 6 | 14 | 13 | 4
Accommodation Abnormal | 0 | 0 | 2 | 0

Table 4 Treatment-Emergent Adverse Event Incidence in Controlled Clinical Studies of Monotherapy in Adults Previously Treated with Other AEDs (Events in at Least 2% of Patients Treated with 2400 mg/day of Trileptal and Numerically More Frequent than in the Low Dose Control Group)
 | Oxcarbazepine Dosage (mg/day)
Body System/ Adverse Event | 2400 N=86 % | 300 N=86 %
Body as a Whole
Fatigue | 21 | 5
Fever | 3 | 0
Allergy | 2 | 0
Edema Generalized | 2 | 1
Pain Chest | 2 | 0
Digestive System
Nausea | 22 | 7
Vomiting | 15 | 5
Diarrhea | 7 | 5
Dyspepsia | 6 | 1
Anorexia | 5 | 3
Pain Abdominal | 5 | 3
Mouth Dry | 3 | 0
Hemorrhage Rectum | 2 | 0
Toothache | 2 | 1
Hemic and Lymphatic System
Lymphadenopathy | 2 | 0
Infections and Infestations
Infection Viral | 7 | 5
Infection | 2 | 0
Metabolic and Nutritional Disorders
Hyponatremia | 5 | 0
Thirst | 2 | 0
Nervous System
Headache | 31 | 15
Dizziness | 28 | 8
Somnolence | 19 | 5
Anxiety | 7 | 5
Ataxia | 7 | 1
Confusion | 7 | 0
Nervousness | 7 | 0
Insomnia | 6 | 3
Tremor | 6 | 3
Amnesia | 5 | 1
Convulsions Aggravated | 5 | 2
Emotional Lability | 3 | 2
Hypoesthesia | 3 | 1
Coordination Abnormal | 2 | 1
Nystagmus | 2 | 0
Speech Disorder | 2 | 0
Respiratory System
Upper Respiratory Tract Infection | 10 | 5
Coughing | 5 | 0
Bronchitis | 3 | 0
Pharyngitis | 3 | 0
Skin and Appendages
Hot Flushes | 2 | 1
Purpura | 2 | 0
Special Senses
Vision Abnormal | 14 | 2
Diplopia | 12 | 1
Taste Perversion | 5 | 0
Vertigo | 3 | 0
Earache | 2 | 1
Ear Infection NOS | 2 | 0
Urogenital and Reproductive System
Urinary Tract Infection | 5 | 1
Micturition Frequency | 2 | 1
Vaginitis | 2 | 0

Controlled Clinical Study of Monotherapy in Adults Not Previously Treated with other AEDs: Table 5 lists treatment-emergent signs and symptoms in a controlled clinical study of monotherapy in adults not previously treated with other AEDs that occurred in at least 2% of adult patients with epilepsy treated with Trileptal or placebo and were numerically more common in the patients treated with Trileptal.

Table 5 Treatment-Emergent Adverse Event Incidence in a Controlled Clinical Study of Monotherapy in Adults Not Previously Treated with Other AEDs (Events in at Least 2% of Patients Treated with Trileptal and Numerically More Frequent than in the Placebo Group)
Body System/ Adverse Event | Oxcarbazepine N=55 % | Placebo N=49 %
Body as a Whole
Falling Down NOS | 4 | 0
Digestive System
Nausea | 16 | 12
Diarrhea | 7 | 2
Vomiting | 7 | 6
Constipation | 5 | 0
Dyspepsia | 5 | 4
Musculoskeletal System
Pain Back | 4 | 2
Nervous System
Dizziness | 22 | 6
Headache | 13 | 10
Ataxia | 5 | 0
Nervousness | 5 | 2
Amnesia | 4 | 2
Coordination Abnormal | 4 | 2
Tremor | 4 | 0
Respiratory System
Upper Respiratory Tract Infection | 7 | 0
Epistaxis | 4 | 0
Infection Chest | 4 | 0
Sinusitis | 4 | 2
Skin and Appendages
Rash | 4 | 2
Special Senses
Vision Abnormal | 4 | 0

Controlled Clinical Studies of Adjunctive Therapy/Monotherapy in Pediatric Patients Previously Treated with other AEDs: Table 6 lists treatment-emergent signs and symptoms that occurred in at least 2% of pediatric patients with epilepsy treated with Trileptal or placebo as adjunctive treatment and were numerically more common in the patients treated with Trileptal.

Table 6 Treatment-Emergent Adverse Event Incidence in Controlled Clinical Studies of Adjunctive Therapy/Monotherapy in Pediatric Patients Previously Treated with Other AEDs (Events in at Least 2% of Patients Treated with Trileptal and Numerically More Frequent than in the Placebo Group)
Body System/ Adverse Event | Oxcarbazepine N=171 % | Placebo N=139 %
Body as a Whole
Fatigue | 13 | 9
Allergy | 2 | 0
Asthenia | 2 | 1
Digestive System
Vomiting | 33 | 14
Nausea | 19 | 5
Constipation | 4 | 1
Dyspepsia | 2 | 0
Nervous System
Headache | 31 | 19
Somnolence | 31 | 13
Dizziness | 28 | 8
Ataxia | 13 | 4
Nystagmus | 9 | 1
Emotional Lability | 8 | 4
Gait Abnormal | 8 | 3
Tremor | 6 | 4
Speech Disorder | 3 | 1
Concentration Impaired | 2 | 1
Convulsions | 2 | 1
Muscle Contractions Involuntary | 2 | 1
Respiratory System
Rhinitis | 10 | 9
Pneumonia | 2 | 1
Skin and Appendages
Bruising | 4 | 2
Sweating Increased | 3 | 0
Special Senses
Diplopia | 17 | 1
Vision Abnormal | 13 | 1
Vertigo | 2 | 0

Other Events Observed in Association with the Administration of Trileptal

In the paragraphs that follow, the adverse events, other than those in the preceding tables or text, that occurred in a total of 565 children and 1,574 adults exposed to Trileptal and that are reasonably likely to be related to drug use are presented. Events common in the population, events reflecting chronic illness and events likely to reflect concomitant illness are omitted particularly if minor. They are listed in order of decreasing frequency. Because the reports cite events observed in open label and uncontrolled trials, the role of Trileptal in their causation cannot be reliably determined.

Body as a Whole: fever, malaise, pain chest precordial, rigors, weight decrease.

Cardiovascular System: bradycardia, cardiac failure, cerebral hemorrhage, hypertension, hypotension postural, palpitation, syncope, tachycardia.

Digestive System: appetite increased, blood in stool, cholelithiasis, colitis, duodenal ulcer, dysphagia, enteritis, eructation, esophagitis, flatulence, gastric ulcer, gingival bleeding, gum hyperplasia, hematemesis, hemorrhage rectum, hemorrhoids, hiccup, mouth dry, pain biliary, pain right hypochondrium, retching, sialoadenitis, stomatitis, stomatitis ulcerative.

Hematologic and Lymphatic System: thrombocytopenia.

Laboratory Abnormality: gamma-GT increased, hyperglycemia, hypocalcemia, hypoglycemia, hypokalemia, liver enzymes elevated, serum transaminase increased.

Musculoskeletal System: hypertonia muscle.

Nervous System: aggressive reaction, amnesia, anguish, anxiety, apathy, aphasia, aura, convulsions aggravated, delirium, delusion, depressed level of consciousness, dysphonia, dystonia, emotional lability, euphoria, extrapyramidal disorder, feeling drunk, hemiplegia, hyperkinesia, hyperreflexia, hypoesthesia, hypokinesia, hyporeflexia, hypotonia, hysteria, libido decreased, libido increased, manic reaction, migraine, muscle contractions involuntary, nervousness, neuralgia, oculogyric crisis, panic disorder, paralysis, paroniria, personality disorder, psychosis, ptosis, stupor, tetany.

Respiratory System: asthma, dyspnea, epistaxis, laryngismus, pleurisy.

Skin and Appendages: acne, alopecia, angioedema, bruising, dermatitis contact, eczema, facial rash, flushing, folliculitis, heat rash, hot flushes, photosensitivity reaction, pruritus genital, psoriasis, purpura, rash erythematous, rash maculopapular, vitiligo, urticaria.

Special Senses: accommodation abnormal, cataract, conjunctival hemorrhage, edema eye, hemianopia, mydriasis, otitis externa, photophobia, scotoma, taste perversion, tinnitus, xerophthalmia.

Surgical and Medical Procedures: procedure dental oral, procedure female reproductive, procedure musculoskeletal, procedure skin.

Urogenital and Reproductive System: dysuria, hematuria, intermenstrual bleeding, leukorrhea, menorrhagia, micturition frequency, pain renal, pain urinary tract, polyuria, priapism, renal calculus.

Other: Systemic lupus erythematosus.

6.2 Post-Marketing and Other Experience

The following adverse events not seen in controlled clinical trials have been observed in named patient programs or post-marketing experience:

Body as a Whole: multi-organ hypersensitivity disorders characterized by features such as rash, fever, lymphadenopathy, abnormal liver function tests, eosinophilia and arthralgia [see Warnings and Precautions (5.8)]

Anaphylaxis: [see Warnings and Precautions (5.2)]

Digestive System: pancreatitis and/or lipase and/or amylase increase

Hematologic and Lymphatic Systems: aplastic anemia [see Warnings and Precautions (5.9)]

Skin and Appendages: erythema multiforme, Stevens-Johnson syndrome, toxic epidermal necrolysis [see Warnings and Precautions (5.4)]

7 DRUG INTERACTIONS

Oxcarbazepine can inhibit CYP2C19 and induce CYP3A4/5 with potentially important effects on plasma concentrations of other drugs. The inhibition of CYP2C19 by oxcarbazepine and MHD can cause increased plasma concentrations of drugs that are substrates of CYP2C19. Oxcarbazepine and MHD induce a subgroup of the cytochrome P450 3A family (CYP3A4 and CYP3A5) responsible for the metabolism of dihydropyridine calcium antagonists, oral contraceptives and cyclosporine resulting in a lower plasma concentration of these drugs. [see Clinical Pharmacology (12.3)]

In addition, several AEDs that are cytochrome P450 inducers can decrease plasma concentrations of oxcarbazepine and MHD. No autoinduction has been observed with Trileptal.

7.1 Antiepileptic Drugs

Potential interactions between Trileptal and other AEDs were assessed in clinical studies. The effect of these interactions on mean AUCs and Cmin are summarized in Table 7.

Table 7 Summary of AED Interactions with Trileptal
AED Coadministered | Dose of AED (mg/day) | Trileptal Dose (mg/day) | Influence of Trileptal on AED Concentration (Mean Change, 90% Confidence Interval) | Influence of AED on MHD Concentration (Mean Change, 90% Confidence Interval)
Carbamazepine | 400-2000 | 900 | nc^1 | 40% decrease [CI: 17% decrease, 57% decrease]
Phenobarbital | 100-150 | 600-1800 | 14% increase [CI: 2% increase, 24% increase] | 25% decrease [CI: 12% decrease, 51% decrease]
Phenytoin | 250-500 | 600-1800 >1200-2400 | nc^1,2 up to 40% increase^3 [CI: 12% increase, 60% increase] | 30% decrease [CI: 3% decrease, 48% decrease]
Valproic acid | 400-2800 | 600-1800 | nc^1 | 18% decrease [CI: 13% decrease, 40% decrease]

^1 nc denotes a mean change of less than 10%

^2 Pediatrics

^3 Mean increase in adults at high Trileptal doses

In vivo, the plasma levels of phenytoin increased by up to 40% when Trileptal was given at doses above 1200 mg/day. Therefore, when using doses of Trileptal greater than 1200 mg/day during adjunctive therapy, a decrease in the dose of phenytoin may be required. The increase of phenobarbital level, however, is small (15%) when given with Trileptal.

Strong inducers of cytochrome P450 enzymes (i.e., carbamazepine, phenytoin and phenobarbital) have been shown to decrease the plasma levels of MHD (29%-40%).

No autoinduction has been observed with Trileptal.

7.2 Hormonal Contraceptives

Coadministration of Trileptal with an oral contraceptive has been shown to influence the plasma concentrations of the two hormonal components, ethinylestradiol (EE) and levonorgestrel (LNG). The mean AUC values of EE were decreased by 48% [90% CI: 22-65] in one study and 52% [90% CI: 38-52] in another study. The mean AUC values of LNG were decreased by 32% [90% CI: 20-45] in one study and 52% [90% CI: 42-52] in another study. Therefore, concurrent use of Trileptal with hormonal contraceptives may render these contraceptives less effective. Studies with other oral or implant contraceptives have not been conducted.

7.3 Calcium Antagonists

After repeated coadministration of Trileptal, the AUC of felodipine was lowered by 28% [90% CI: 20-33]. Verapamil produced a decrease of 20% [90% CI: 18-27] of the plasma levels of MHD.

7.4 Other Drug Interactions

Cimetidine, erythromycin and dextropropoxyphene had no effect on the pharmacokinetics of MHD. Results with warfarin show no evidence of interaction with either single or repeated doses of Trileptal.

7.5 Drug/Laboratory Test Interactions

There are no known interactions of Trileptal with commonly used laboratory tests.

8 USE IN SPECIFIC POPULATIONS

8.1 Pregnancy

Trileptal levels may decrease during pregnancy [see Warnings and Precautions (5.10)].

Pregnancy Category C

There are no adequate and well-controlled clinical studies of Trileptal in pregnant women; however, Trileptal is closely related structurally to carbamazepine, which is considered to be teratogenic in humans. Given this fact, and the results of the animal studies described, it is likely that Trileptal is a human teratogen. Trileptal should be used during pregnancy only if the potential benefit justifies the potential risk to the fetus.

Increased incidences of fetal structural abnormalities and other manifestations of developmental toxicity (embryolethality, growth retardation) were observed in the offspring of animals treated with either oxcarbazepine or its active 10-hydroxy metabolite (MHD) during pregnancy at doses similar to the maximum recommended human dose.

When pregnant rats were given oxcarbazepine (30, 300, or 1000 mg/kg) orally throughout the period of organogenesis, increased incidences of fetal malformations (craniofacial, cardiovascular, and skeletal) and variations were observed at the intermediate and high doses (approximately 1.2 and 4 times, respectively, the maximum recommended human dose [MRHD] on a mg/m^2 basis). Increased embryofetal death and decreased fetal body weights were seen at the high dose. Doses ≥300 mg/kg were also maternally toxic (decreased body weight gain, clinical signs), but there is no evidence to suggest that teratogenicity was secondary to the maternal effects.

In a study in which pregnant rabbits were orally administered MHD (20, 100, or 200 mg/kg) during organogenesis, embryofetal mortality was increased at the highest dose (1.5 times the MRHD on a mg/m^2 basis). This dose produced only minimal maternal toxicity.

In a study in which female rats were dosed orally with oxcarbazepine (25, 50, or 150 mg/kg) during the latter part of gestation and throughout the lactation period, a persistent reduction in body weights and altered behavior (decreased activity) were observed in offspring exposed to the highest dose (0.6 times the MRHD on a mg/m^2 basis). Oral administration of MHD (25, 75, or 250 mg/kg) to rats during gestation and lactation resulted in a persistent reduction in offspring weights at the highest dose (equivalent to the MRHD on a mg/m^2 basis).

To provide information regarding the effects of in utero exposure to Trileptal, physicians are advised to recommend that pregnant patients taking Trileptal enroll in the NAAED Pregnancy Registry. This can be done by calling the toll free number 1-888-233-2334, and must be done by patients themselves. Information on the registry can also be found at the website http://www.aedpregnancyregistry.org/.

8.2 Labor and Delivery

The effect of Trileptal on labor and delivery in humans has not been evaluated.

8.3 Nursing Mothers

Oxcarbazepine and its active metabolite (MHD) are excreted in human milk. A milk-to-plasma concentration ratio of 0.5 was found for both. Because of the potential for serious adverse reactions to Trileptal in nursing infants, a decision should be made about whether to discontinue nursing or to discontinue the drug in nursing women, taking into account the importance of the drug to the mother.

8.4 Pediatric Use

Trileptal is indicated for use as adjunctive therapy for partial seizures in patients aged 2-16 years. Trileptal is also indicated as monotherapy for partial seizures in patients aged 4-16 years. Trileptal has been given to 898 patients between the ages of 1 month-17 years in controlled clinical trials (332 treated as monotherapy) and about 677 patients between the ages of 1 month-17 years in other trials [see Adverse Reactions (6.1) for a description of the adverse events associated with Trileptal use in this population].

8.5 Geriatric Use

There were 52 patients over age 65 in controlled clinical trials and 565 patients over the age of 65 in other trials. Following administration of single (300 mg) and multiple (600 mg/day) doses of Trileptal in elderly volunteers (60-82 years of age), the maximum plasma concentrations and AUC values of MHD were 30%-60% higher than in younger volunteers (18-32 years of age). Comparisons of creatinine clearance in young and elderly volunteers indicate that the difference was due to age-related reductions in creatinine clearance.

8.6 Renal Impairment

In renally-impaired patients (creatinine clearance <30 mL/min), the elimination half-life of MHD is prolonged with a corresponding two-fold increase in AUC [see Clinical Pharmacology (12.3)]. Trileptal therapy should be initiated at one-half the usual starting dose and increased, if necessary, at a slower than usual rate until the desired clinical response is achieved.

9 DRUG ABUSE AND DEPENDENCE

9.2 Abuse

The abuse potential of Trileptal has not been evaluated in human studies.

9.3 Dependence

Intragastric injections of oxcarbazepine to four cynomolgus monkeys demonstrated no signs of physical dependence as measured by the desire to self-administer oxcarbazepine by lever pressing activity.

10 OVERDOSAGE

Human Overdose Experience

Isolated cases of overdose with Trileptal have been reported. The maximum dose taken was approximately 24,000 mg. All patients recovered with symptomatic treatment.

Treatment and Management

There is no specific antidote. Symptomatic and supportive treatment should be administered as appropriate. Removal of the drug by gastric lavage and/or inactivation by administering activated charcoal should be considered.

11 DESCRIPTION

Trileptal is an antiepileptic drug available as 150 mg, 300 mg and 600 mg film-coated tablets for oral administration. Trileptal is also available as a 300 mg/5 mL (60 mg/mL) oral suspension. Oxcarbazepine is 10,11-Dihydro-10-oxo-5H-dibenz[b,f]azepine-5-carboxamide, and its structural formula is

Oxcarbazepine is a white to faintly orange crystalline powder. It is slightly soluble in chloroform, dichloromethane, acetone, and methanol and practically insoluble in ethanol, ether and water. Its molecular weight is 252.27.

Trileptal film-coated tablets contain the following inactive ingredients: colloidal silicon dioxide, crospovidone, hydroxypropyl methylcellulose, iron oxide, magnesium stearate, microcrystalline cellulose, polyethylene glycol, talc and titanium dioxide.

Trileptal oral suspension contains the following inactive ingredients: ascorbic acid; dispersible cellulose; ethanol; macrogol stearate; methyl parahydroxybenzoate; propylene glycol; propyl parahydroxybenzoate; purified water; sodium saccharin; sorbic acid; sorbitol; yellow-plum-lemon aroma.

12 CLINICAL PHARMACOLOGY

12.1 Mechanism of Action

The pharmacological activity of Trileptal is primarily exerted through the 10-monohydroxy metabolite (MHD) of oxcarbazepine [see Clinical Pharmacology (12.3)]. The precise mechanism by which oxcarbazepine and MHD exert their antiseizure effect is unknown; however, in vitro electrophysiological studies indicate that they produce blockade of voltage-sensitive sodium channels, resulting in stabilization of hyperexcited neural membranes, inhibition of repetitive neuronal firing, and diminution of propagation of synaptic impulses. These actions are thought to be important in the prevention of seizure spread in the intact brain. In addition, increased potassium conductance and modulation of high-voltage activated calcium channels may contribute to the anticonvulsant effects of the drug. No significant interactions of oxcarbazepine or MHD with brain neurotransmitter or modulator receptor sites have been demonstrated.

12.2 Pharmacodynamics

Oxcarbazepine and its active metabolite (MHD) exhibit anticonvulsant properties in animal seizure models. They protected rodents against electrically induced tonic extension seizures and, to a lesser degree, chemically induced clonic seizures, and abolished or reduced the frequency of chronically recurring focal seizures in Rhesus monkeys with aluminum implants. No development of tolerance (i.e., attenuation of anticonvulsive activity) was observed in the maximal electroshock test when mice and rats were treated daily for five days and four weeks, respectively, with oxcarbazepine or MHD.

12.3 Pharmacokinetics

Following oral administration of Trileptal tablets, oxcarbazepine is completely absorbed and extensively metabolized to its pharmacologically active 10-monohydroxy metabolite (MHD). In a mass balance study in people, only 2% of total radioactivity in plasma was due to unchanged oxcarbazepine, with approximately 70% present as MHD, and the remainder attributable to minor metabolites.

The half-life of the parent is about two hours, while the half-life of MHD is about nine hours, so that MHD is responsible for most antiepileptic activity.

Absorption

Based on MHD concentrations, Trileptal tablets and suspension were shown to have similar bioavailability.

After single-dose administration of Trileptal tablets to healthy male volunteers under fasted conditions, the median tmax was 4.5 (range 3 to 13) hours. After single-dose administration of Trileptal oral suspension to healthy male volunteers under fasted conditions, the median tmax was six hours.

Steady-state plasma concentrations of MHD are reached within 2-3 days in patients when Trileptal is given twice a day. At steady state the pharmacokinetics of MHD are linear and show dose proportionality over the dose range of 300 to 2400 mg/day.

Effect of Food: Food has no effect on the rate and extent of absorption of oxcarbazepine from Trileptal tablets. Although not directly studied, the oral bioavailability of the Trileptal suspension is unlikely to be affected under fed conditions. Therefore, Trileptal tablets and suspension can be taken with or without food.

Distribution

The apparent volume of distribution of MHD is 49L.

Approximately 40% of MHD is bound to serum proteins, predominantly to albumin. Binding is independent of the serum concentration within the therapeutically relevant range. Oxcarbazepine and MHD do not bind to alpha-1-acid glycoprotein.

Metabolism and Excretion

Oxcarbazepine is rapidly reduced by cytosolic enzymes in the liver to its 10-monohydroxy metabolite, MHD, which is primarily responsible for the pharmacological effect of Trileptal. MHD is metabolized further by conjugation with glucuronic acid. Minor amounts (4% of the dose) are oxidized to the pharmacologically inactive 10,11-dihydroxy metabolite (DHD).

Oxcarbazepine is cleared from the body mostly in the form of metabolites which are predominantly excreted by the kidneys. More than 95% of the dose appears in the urine, with less than 1% as unchanged oxcarbazepine. Fecal excretion accounts for less than 4% of the administered dose. Approximately 80% of the dose is excreted in the urine either as glucuronides of MHD (49%) or as unchanged MHD (27%); the inactive DHD accounts for approximately 3% and conjugates of MHD and oxcarbazepine account for 13% of the dose.

The half-life of the parent is about two hours, while the half-life of MHD is about nine hours.

Special Populations

Hepatic Impairment

The pharmacokinetics and metabolism of oxcarbazepine and MHD were evaluated in healthy volunteers and hepatically-impaired subjects after a single 900-mg oral dose. Mild-to-moderate hepatic impairment did not affect the pharmacokinetics of oxcarbazepine and MHD. No dose adjustment for Trileptal is recommended in patients with mild-to-moderate hepatic impairment. The pharmacokinetics of oxcarbazepine and MHD have not been evaluated in severe hepatic impairment and, therefore, caution should be exercised when dosing severely impaired patients [see Dosage and Administration (2.7)].

Renal Impairment

There is a linear correlation between creatinine clearance and the renal clearance of MHD. When Trileptal is administered as a single 300-mg dose in renally-impaired patients (creatinine clearance <30 mL/min), the elimination half-life of MHD is prolonged to 19 hours, with a two-fold increase in AUC. Dose adjustment for Trileptal is recommended in these patients [see Use in Specific Populations (8.6) and see Dosage and Administration (2.8)].

Pediatrics

Weight-adjusted MHD clearance decreases as age and weight increases, approaching that of adults. The mean weight-adjusted clearance in children 2 years-<4 years of age is approximately 80% higher on average than that of adults. Therefore, MHD exposure in these children is expected to be about one-half that of adults when treated with a similar weight-adjusted dose. The mean weight-adjusted clearance in children 4–12 years of age is approximately 40% higher on average than that of adults. Therefore, MHD exposure in these children is expected to be about three-quarters that of adults when treated with a similar weight-adjusted dose. As weight increases, for patients 13 years of age and above, the weight-adjusted MHD clearance is expected to reach that of adults.

Pregnancy

Due to physiological changes during pregnancy, MHD plasma levels may gradually decrease throughout pregnancy [see Use in Specific Populations (8.1)]

Geriatrics

Following administration of single (300 mg) and multiple (600 mg/day) doses of Trileptal to elderly volunteers (60-82 years of age), the maximum plasma concentrations and AUC values of MHD were 30%-60% higher than in younger volunteers (18-32 years of age). Comparisons of creatinine clearance in young and elderly volunteers indicate that the difference was due to age-related reductions in creatinine clearance.

Gender

No gender-related pharmacokinetic differences have been observed in children, adults, or the elderly.

Race

No specific studies have been conducted to assess what effect, if any, race may have on the disposition of oxcarbazepine.

Drug Interactions:

In Vitro

Oxcarbazepine can inhibit CYP2C19 and induce CYP3A4/5 with potentially important effects on plasma concentrations of other drugs. In addition, several AEDs that are cytochrome P450 inducers can decrease plasma concentrations of oxcarbazepine and MHD.

Oxcarbazepine was evaluated in human liver microsomes to determine its capacity to inhibit the major cytochrome P450 enzymes responsible for the metabolism of other drugs. Results demonstrate that oxcarbazepine and its pharmacologically active 10-monohydroxy metabolite (MHD) have little or no capacity to function as inhibitors for most of the human cytochrome P450 enzymes evaluated (CYP1A2, CYP2A6, CYP2C9, CYP2D6, CYP2E1, CYP4A9 and CYP4A11) with the exception of CYP2C19 and CYP3A4/5. Although inhibition of CYP3A4/5 by oxcarbazepine and MHD did occur at high concentrations, it is not likely to be of clinical significance. The inhibition of CYP2C19 by oxcarbazepine and MHD, is clinically relevant.

In vitro, the UDP-glucuronyl transferase level was increased, indicating induction of this enzyme. Increases of 22% with MHD and 47% with oxcarbazepine were observed. As MHD, the predominant plasma substrate, is only a weak inducer of UDP-glucuronyl transferase, it is unlikely to have an effect on drugs that are mainly eliminated by conjugation through UDP-glucuronyl transferase (e.g., valproic acid, lamotrigine).

In addition, oxcarbazepine and MHD induce a subgroup of the cytochrome P450 3A family (CYP3A4 and CYP3A5) responsible for the metabolism of dihydropyridine calcium antagonists, oral contraceptives and cyclosporine resulting in a lower plasma concentration of these drugs.

As binding of MHD to plasma proteins is low (40%), clinically significant interactions with other drugs through competition for protein binding sites are unlikely.

In Vivo

For in vivo drug interactions [see Drug Interactions (7)].

13 NONCLINICAL TOXICOLOGY

13.1 Carcinogenesis, Mutagenesis, Impairment of Fertility

Carcinogenesis

In two-year carcinogenicity studies, oxcarbazepine was administered in the diet at doses of up to 100 mg/kg/day to mice and by gavage at doses of up to 250 mg/kg/day to rats, and the pharmacologically active 10-hydroxy metabolite (MHD) was administered orally at doses of up to 600 mg/kg/day to rats. In mice, a dose-related increase in the incidence of hepatocellular adenomas was observed at oxcarbazepine doses ≥70 mg/kg/day or approximately 0.1 times the maximum recommended human dose (MRHD) on a mg/m^2 basis. In rats, the incidence of hepatocellular carcinomas was increased in females treated with oxcarbazepine at doses ≥25 mg/kg/day (0.1 times the MRHD on a mg/m^2 basis), and incidences of hepatocellular adenomas and/or carcinomas were increased in males and females treated with MHD at doses of 600 mg/kg/day (2.4 times the MRHD on a mg/m^2 basis) and ≥250 mg/kg/day (equivalent to the MRHD on a mg/m^2 basis), respectively. There was an increase in the incidence of benign testicular interstitial cell tumors in rats at 250 mg oxcarbazepine/kg/day and at ≥250 mg MHD/kg/day, and an increase in the incidence of granular cell tumors in the cervix and vagina in rats at 600 mg MHD/kg/day.

Mutagenesis

Oxcarbazepine increased mutation frequencies in the Ames test in vitro in the absence of metabolic activation in one of five bacterial strains. Both oxcarbazepine and MHD produced increases in chromosomal aberrations and polyploidy in the Chinese hamster ovary assay in vitro in the absence of metabolic activation. MHD was negative in the Ames test, and no mutagenic or clastogenic activity was found with either oxcarbazepine or MHD in V79 Chinese hamster cells in vitro. Oxcarbazepine and MHD were both negative for clastogenic or aneugenic effects (micronucleus formation) in an in vivo rat bone marrow assay.

Impairment of Fertility

In a fertility study in which rats were administered MHD (50, 150, or 450 mg/kg) orally prior to and during mating and early gestation, estrous cyclicity was disrupted and numbers of corpora lutea, implantations, and live embryos were reduced in females receiving the highest dose (approximately two times the MRHD on a mg/m^2 basis).

14 CLINICAL STUDIES

The effectiveness of Trileptal as adjunctive and monotherapy for partial seizures in adults, and as adjunctive therapy in children aged 2-16 years was established in seven multicenter, randomized, controlled trials.

The effectiveness of Trileptal as monotherapy for partial seizures in children aged 4-16 years was determined from data obtained in the studies described, as well as by pharmacokinetic/pharmacodynamic considerations.

14.1 Trileptal Monotherapy Trials

Four randomized, controlled, double-blind, multicenter trials, conducted in a predominately adult population, demonstrated the efficacy of Trileptal as monotherapy. Two trials compared Trileptal to placebo and two trials used a randomized withdrawal design to compare a high dose (2400 mg) with a low dose (300 mg) of Trileptal, after substituting Trileptal 2400 mg/day for one or more antiepileptic drugs (AEDs). All doses were administered on a twice-a-day schedule. A fifth randomized, controlled, rater-blind, multicenter study, conducted in a pediatric population, failed to demonstrate a statistically significant difference between low and high dose Trileptal treatment groups.

One placebo-controlled trial was conducted in 102 patients (11-62 years of age) with refractory partial seizures who had completed an inpatient evaluation for epilepsy surgery. Patients had been withdrawn from all AEDs and were required to have 2-10 partial seizures within 48 hours prior to randomization. Patients were randomized to receive either placebo or Trileptal given as 1500 mg/day on Day 1 and 2400 mg/day thereafter for an additional nine days, or until one of the following three exit criteria occurred: 1) the occurrence of a fourth partial seizure, excluding Day 1, 2) two new-onset secondarily generalized seizures, where such seizures were not seen in the one-year period prior to randomization, or 3) occurrence of serial seizures or status epilepticus. The primary measure of effectiveness was a between-group comparison of the time to meet exit criteria. There was a statistically significant difference in favor of Trileptal (see Figure 1), p=0.0001.

Figure 1 Kaplan-Meier Estimates of Exit Rate by Treatment Group

The second placebo-controlled trial was conducted in 67 untreated patients (8-69 years of age) with newly-diagnosed and recent-onset partial seizures. Patients were randomized to placebo or Trileptal, initiated at 300 mg twice a day and titrated to 1200 mg/day (given as 600 mg twice a day) in six days, followed by maintenance treatment for 84 days. The primary measure of effectiveness was a between-group comparison of the time to first seizure. The difference between the two treatments was statistically significant in favor of Trileptal (see Figure 2), p=0.046.

Figure 2 Kaplan-Meier Estimates of First Seizure Event Rate by Treatment Group

A third trial substituted Trileptal monotherapy at 2400 mg/day for carbamazepine in 143 patients (12-65 years of age) whose partial seizures were inadequately controlled on carbamazepine (CBZ) monotherapy at a stable dose of 800 to 1600 mg/day, and maintained this Trileptal dose for 56 days (baseline phase). Patients who were able to tolerate titration of Trileptal to 2400 mg/day during simultaneous carbamazepine withdrawal were randomly assigned to either 300 mg/day of Trileptal or 2400 mg/day Trileptal. Patients were observed for 126 days or until one of the following four exit criteria occurred: 1) a doubling of the 28-day seizure frequency compared to baseline, 2) a two-fold increase in the highest consecutive two-day seizure frequency during baseline, 3) a single generalized seizure if none had occurred during baseline, or 4) a prolonged generalized seizure. The primary measure of effectiveness was a between-group comparison of the time to meet exit criteria. The difference between the curves was statistically significant in favor of the Trileptal 2400 mg/day group (see Figure 3), p=0.0001.

Figure 3 Kaplan-Meier Estimates of Exit Rate by Treatment Group

Another monotherapy substitution trial was conducted in 87 patients (11-66 years of age) whose seizures were inadequately controlled on one or two AEDs. Patients were randomized to either Trileptal 2400 mg/day or 300 mg/day and their standard AED regimen(s) were eliminated over the first six weeks of double-blind therapy. Double-blind treatment continued for another 84 days (total double-blind treatment of 126 days) or until one of the four exit criteria described for the previous study occurred. The primary measure of effectiveness was a between-group comparison of the percentage of patients meeting exit criteria. The results were statistically significant in favor of the Trileptal 2400 mg/day group (14/34; 41.2%) compared to the Trileptal 300 mg/day group (42/45; 93.3%) (p<0.0001). The time to meeting one of the exit criteria was also statistically significant in favor of the Trileptal 2400 mg/day group (see Figure 4), p=0.0001.

Figure 4 Kaplan-Meier Estimates of Exit Rate by Treatment Group

A monotherapy trial was conducted in 92 pediatric patients (1 month to 16 years of age) with inadequately-controlled or new-onset partial seizures. Patients were hospitalized and randomized to either Trileptal 10 mg/kg/day or were titrated up to 40-60 mg/kg/day within three days while withdrawing the previous AED on the second day of Trileptal therapy. Seizures were recorded through continuous video-EEG monitoring from Day 3 to Day 5. Patients either completed the 5-day treatment or met one of the two exit criteria: 1) three study-specific seizures (i.e., electrographic partial seizures with a behavioral correlate), 2) a prolonged study-specific seizure. The primary measure of effectiveness was a between-group comparison of the time to meet exit criteria in which the difference between the curves was not statistically significant (p=0.904). The majority of patients from both dose groups completed the 5-day study without exiting.

Although this study failed to demonstrate an effect of oxcarbazepine as monotherapy in pediatric patients, several design elements, including the short treatment and assessment period, the absence of a true placebo, and the likely persistence of plasma levels of previously administered AEDs during the treatment period, make the results uninterpretable. For this reason, the results do not undermine the conclusion, based on pharmacokinetic/pharmacodynamic considerations, that oxcarbazepine is effective as monotherapy in pediatric patients 4 years old and older.

14.2 Trileptal Adjunctive Therapy Trials

The effectiveness of Trileptal as an adjunctive therapy for partial seizures was established in two multicenter, randomized, double-blind, placebo-controlled trials, one in 692 patients (15-66 years of age) and one in 264 pediatric patients (3-17 years of age), and in one multicenter, rater-blind, randomized, age-stratified, parallel-group study comparing two doses of oxcarbazepine in 128 pediatric patients (1 month to <4 years of age).

Patients in the two placebo-controlled trials were on 1-3 concomitant AEDs. In both of the trials, patients were stabilized on optimum dosages of their concomitant AEDs during an 8-week baseline phase. Patients who experienced at least 8 (minimum of 1-4 per month) partial seizures during the baseline phase were randomly assigned to placebo or to a specific dose of Trileptal in addition to their other AEDs.

In these studies, the dose was increased over a two-week period until either the assigned dose was reached, or intolerance prevented increases. Patients then entered a 14- (pediatrics) or 24-week (adults) maintenance period.

In the adult trial, patients received fixed doses of 600, 1200 or 2400 mg/day. In the pediatric trial, patients received maintenance doses in the range of 30-46 mg/kg/day, depending on baseline weight. The primary measure of effectiveness in both trials was a between-group comparison of the percentage change in partial seizure frequency in the double-blind treatment phase relative to baseline phase. This comparison was statistically significant in favor of Trileptal at all doses tested in both trials (p=0.0001 for all doses for both trials). The number of patients randomized to each dose, the median baseline seizure rate, and the median percentage seizure rate reduction for each trial are shown in Table 8. It is important to note that in the high-dose group in the study in adults, over 65% of patients discontinued treatment because of adverse events; only 46 (27%) of the patients in this group completed the 28-week study [see Adverse Reactions (7)], an outcome not seen in the monotherapy studies.

Table 8 Summary of Percentage Change in Partial Seizure Frequency from Baseline for Placebo-Controlled Adjunctive Therapy Trials
Trial | Treatment Group
 |  | N |  | Baseline Median Seizure Rate* |  | Median % Reduction
1 (pediatrics) | Trileptal | 136 |  | 12.5 |  | 34.8^1
 | Placebo | 128 |  | 13.1 |  | 9.4
2 (adults) | Trileptal 2400 mg/day | 174 |  | 10.0 |  | 49.9^1
 | Trileptal 1200 mg/day | 177 |  | 9.8 |  | 40.2^1
 | Trileptal 600 mg/day | 168 |  | 9.6 |  | 26.4^1
 | Placebo | 173 |  | 8.6 |  | 7.6

^1 p=0.0001; * = # per 28 days

Subset analyses of the antiepileptic efficacy of Trileptal with regard to gender in these trials revealed no important differences in response between men and women. Because there were very few patients over the age of 65 in controlled trials, the effect of the drug in the elderly has not been adequately assessed.

The third adjunctive therapy trial enrolled 128 pediatric patients (1 month to <4 years of age) with inadequately-controlled partial seizures on 1-2 concomitant AEDs. Patients who experienced at least 2 study-specific seizures (i.e., electrographic partial seizures with a behavioral correlate) during the 72-hour baseline period were randomly assigned to either Trileptal 10 mg/kg/day or were titrated up to 60 mg/kg/day within 26 days. Patients were maintained on their randomized target dose for 9 days and seizures were recorded through continuous video-EEG monitoring during the last 72 hours of the maintenance period. The primary measure of effectiveness in this trial was a between-group comparison of the change in seizure frequency per 24 hours compared to the seizure frequency at baseline. For the entire group of patients enrolled, this comparison was statistically significant in favor of Trileptal 60 mg/kg/day. In this study, there was no evidence that Trileptal was effective in patients below the age of 2 years (N=75).

16 HOW SUPPLIED/STORAGE AND HANDLING

Tablets

150 mg Film-Coated Tablets: pale grey-green, ovaloid, slightly biconvex, scored on both sides. Imprinted with T/D on one side and C/G on the other side.

Bottle of 10.……………………………………………………………………………………………...NDC 54868-4836-3

Bottle of 20.……………………………………………………………………………………………...NDC 54868-4836-1
Bottle of 30.……………………………………………………………………………………………...NDC 54868-4836-4
Bottle of 60.……………………………………………………………………………………………...NDC 54868-4836-0

300 mg Film-Coated Tablets: yellow, ovaloid, slightly biconvex, scored on both sides. Imprinted with TE/TE on one side and CG/CG on the other side.

Bottle of 20.……………………………………………………………………………………………...NDC 54868-4837-1

Bottle of 300……………………………………………………………………………………………...NDC 54868-4837-3

Store at 25°C (77°F); excursions permitted to 15-30°C (59-86°F) [see USP Controlled Room Temperature]. Dispense in tight container (USP).

17 PATIENT COUNSELING INFORMATION

Patients and caregivers should be informed of the availability of a Medication Guide, and they should be instructed to read the Medication Guide prior to taking Trileptal.

Patients should be advised that Trileptal may reduce the serum sodium concentrations especially if they are taking other medications that can lower sodium. Patients should be advised to report symptoms of low sodium like nausea, tiredness, lack of energy, confusion, and more frequent or more severe seizures [see Warnings and Precautions (5.1)].

Anaphylactic reactions and angioedema may occur during treatment with Trileptal. Patients should be advised to report immediately signs and symptoms suggesting angioedema (swelling of the face, eyes, lips, tongue or difficulty in swallowing or breathing) and to stop taking the drug until they have consulted with their physician [see Warnings and Precautions (5.2)].

Patients who have exhibited hypersensitivity reactions to carbamazepine should be informed that approximately 25%-30% of these patients may experience hypersensitivity reactions with Trileptal. Patients should be advised that if they experience a hypersensitivity reaction while taking Trileptal they should consult with their physician immediately [see Warnings and Precautions (5.3)].

Patients should be advised that serious skin reactions have been reported in association with Trileptal. In the event a skin reaction should occur while taking Trileptal, patients should consult with their physician immediately [see Warnings and Precautions (5.4)].

Patients should be instructed that a fever associated with other organ system involvement (rash, lymphadenopathy, etc.) may be drug related and should be reported to the physician immediately [see Warnings and Precautions (5.8)].

Patients should be advised that there have been rare reports of blood disorders reported in patients treated with Trileptal. Patients should be instructed to immediately consult with their physician if they experience symptoms suggestive of blood disorders [see Warnings and Precautions (5.9)].

Female patients of childbearing age should be warned that the concurrent use of Trileptal with hormonal contraceptives may render this method of contraception less effective [see Drug Interactions (7.2)]. Additional non-hormonal forms of contraception are recommended when using Trileptal.

Patients, their caregivers, and families should be counseled that AEDs, including Trileptal, may increase the risk of suicidal thoughts and behavior and should be advised of the need to be alert for the emergence or worsening of symptoms of depression, any unusual changes in mood or behavior, or the emergence of suicidal thoughts, behavior, or thoughts about self-harm. Behaviors of concern should be reported immediately to healthcare providers.

Caution should be exercised if alcohol is taken in combination with Trileptal therapy, due to a possible additive sedative effect.

Patients should be advised that Trileptal may cause dizziness and somnolence. Accordingly, patients should be advised not to drive or operate machinery until they have gained sufficient experience on Trileptal to gauge whether it adversely affects their ability to drive or operate machinery.

Patients should be encouraged to enroll in the North American Antiepileptic Drug (NAAED) Pregnancy Registry if they become pregnant. This registry is collecting information about the safety of antiepileptic drugs during pregnancy. To enroll, patients can call the toll free number 1-888-233-2334 [see Use in Specific Populations (8.1)].

MEDICATION GUIDE

TRILEPTAL® (try-LĔP-tăl)

(oxcarbazepine)

Tablets and Oral Suspension

Read this Medication Guide before you start taking TRILEPTAL and each time you get a refill. There may be new information. This information does not take the place of talking to your healthcare provider about your medical condition or treatment.

What is the most important information I should know about TRILEPTAL?

Do not stop taking TRILEPTAL without first talking to your healthcare provider.

Stopping TRILEPTAL suddenly can cause serious problems.

TRILEPTAL can cause serious side effects, including:

1. TRILEPTAL may cause the level of sodium in your blood to be low. Symptoms of low blood sodium include:

- nausea
- tiredness, lack of energy
- headache
- confusion
- more frequent or more severe seizures.

Similar symptoms that are not related to low sodium may occur from taking TRILEPTAL. You should tell your healthcare provider if you have any of these side effects and if they bother you or they do not go away.

Some other medicines can also cause low sodium in your blood. Be sure to tell your healthcare provider about all the other medicines that you are taking.

2. TRILEPTAL may also cause allergic reactions or serious problems which may affect organs and other parts of your body like the liver or blood cells. You may or may not have a rash with these types of reactions.
Call your healthcare provider right away if you have any of the following:

- swelling of your face, eyes, lips, or tongue
- trouble swallowing or breathing
- a skin rash
- hives
- fever, swollen glands, or sore throat that do not go away or come and go
- painful sores in the mouth or around your eyes
- yellowing of your skin or eyes
- unusual bruising or bleeding
- severe fatigue or weakness
- severe muscle pain
- frequent infections or infections that do not go away

Many people who are allergic to carbamazepine are also allergic to TRILEPTAL. Tell your healthcare provider if you are allergic to carbamazepine.

3. Like other antiepileptic drugs, TRILEPTAL may cause suicidal thoughts or actions in a very small number of people, about 1 in 500.
Call a doctor right away if you have any of these symptoms, especially if they are new, worse, or worry you:

- thoughts about suicide or dying
- attempts to commit suicide
- new or worse depression
- new or worse anxiety
- feeling agitated or restless
- panic attacks
- trouble sleeping (insomnia)
- new or worse irritability
- acting aggressive, being angry, or violent
- acting on dangerous impulses
- an extreme increase in activity and talking (mania)
- other unusual changes in behavior or mood

How can I watch for early symptoms of suicidal thoughts and actions?

- Pay attention to any changes, especially sudden changes, in mood, behaviors, thoughts, or feelings.
- Keep all follow-up visits with your healthcare provider as scheduled.

Call your healthcare provider between visits as needed, especially if you are worried about symptoms.

Do not stop taking TRILEPTAL without first talking to a healthcare provider.

Stopping TRILEPTAL suddenly can cause serious problems. Stopping a seizure medicine suddenly in a patient who has epilepsy may cause seizures that will not stop (status epilepticus).

Suicidal thoughts or actions may be caused by things other than medicines. If you have suicidal thoughts or actions, your healthcare provider may check for other causes.

What is TRILEPTAL?

TRILEPTAL is a prescription medicine used:

- alone or with other medicines to treat partial seizures in adults.
- alone to treat partial seizures in children 4 years and older.
- with other medicines to treat partial seizures in children 2 years and older.

Who should not take TRILEPTAL?

- Do not take TRILEPTAL if you are allergic to TRILEPTAL or any of the other ingredients in TRILEPTAL. See the end of this leaflet for a complete list of ingredients in TRILEPTAL.
- Many people who are allergic to carbamazepine are also allergic to TRILEPTAL. Tell your healthcare provider if you are allergic to carbamazepine.

What should I tell my healthcare provider before taking TRILEPTAL?

Before taking TRILEPTAL, tell your healthcare provider about all your medical conditions, including if you:

- have or have had suicidal thoughts or actions, depression or mood problems
- have liver problems
- have kidney problems
- are allergic to carbamazepine. Many people who are allergic to carbamazepine are also allergic to TRILEPTAL.
- use birth control medicine. TRILEPTAL may cause your birth control medicine to be less effective. Talk to your healthcare provider about the best birth control method to use.
- are pregnant or plan to become pregnant. TRILEPTAL may harm your unborn baby. Tell your healthcare provider right away if you become pregnant while taking TRILEPTAL. You and your healthcare provider will decide if you should take TRILEPTAL while you are pregnant.
  ○ If you become pregnant while taking TRILEPTAL, talk to your healthcare provider about registering with the North American Antiepileptic Drug (NAAED) Pregnancy Registry. The purpose of this registry is to collect information about the safety of antiepileptic medicine during pregnancy. You can enroll in this registry by calling 1-888-233-2334.
- are breastfeeding or plan to breastfeed. TRILEPTAL passes into breast milk. You and your healthcare provider should discuss whether you should take TRILEPTAL or breastfeed; you should not do both.

Tell your healthcare provider about all the medicines you take, including prescription and non-prescription medicines, vitamins, and herbal supplements.

Taking TRILEPTAL with certain other medicines may cause side effects or affect how well they work. Do not start or stop other medicines without talking to your healthcare provider.

Know the medicines you take. Keep a list of them and show it to your healthcare provider and pharmacist when you get a new medicine.

How should I take TRILEPTAL?

- Do not stop taking TRILEPTAL without talking to your healthcare provider. Stopping TRILEPTAL suddenly can cause serious problems, including seizures that will not stop (status epilepticus).
- Take TRILEPTAL exactly as prescribed. Your healthcare provider may change your dose. Your healthcare provider will tell you how much TRILEPTAL to take.
- Take TRILEPTAL 2 times a day.
- Take TRILEPTAL with or without food.
- Before taking TRILEPTAL oral suspension shake the bottle well and use the oral dosing syringe to measure the amount of medicine needed. TRILEPTAL oral suspension can be mixed in a small glass of water, or swallowed directly from the syringe. Clean the syringe with warm water and let it dry after each use.
- If you take too much TRILEPTAL, call your healthcare provider or local Poison Control Center right away.

What should I avoid while taking TRILEPTAL?

- Do not drive, operate heavy machinery, or do other dangerous activities until you know how TRILEPTAL affects you. TRILEPTAL may slow your thinking and motor skills.
- Do not drink alcohol or take other drugs that make you sleepy or dizzy while taking TRILEPTAL until you talk to your healthcare provider. TRILEPTAL taken with alcohol or drugs that cause sleepiness or dizziness may make your sleepiness or dizziness worse.

What are the possible side effects of TRILEPTAL?

See “What is the most important information I should know about TRILEPTAL?”

TRILEPTAL may cause other serious side effects including:

- your seizures can happen more often or become worse
- trouble concentrating
- problems with your speech and language
- feeling confused
- feeling sleepy and tired
- trouble walking and with coordination

Get medical help right away if you have any of the symptoms listed above or listed in “What is the most important information I should know about TRILEPTAL?”

The most common side effects of TRILEPTAL include:

- dizziness
- sleepiness
- double vision
- tiredness
- nausea
- vomiting
- problems with vision
- stomach pain
- trembling
- upset stomach
- problems with walking and coordination (unsteadiness)
- rash
- infections (especially in children)

These are not all the possible side effects of TRILEPTAL. For more information, ask your healthcare provider or pharmacist. Tell your healthcare provider if you have any side effect that bothers you or does not go away

Call your doctor for medical advice about side effects. You may report side effects to FDA at 1-800-FDA-1088.

How should I store TRILEPTAL?

- Store TRILEPTAL Tablets and Oral Suspension between 15°C to 30°C (59°F to 86°F)
  ○ Keep TRILEPTAL tablets dry.
  ○ Keep TRILEPTAL oral suspension in the original container. Use within 7 weeks of first opening the bottle. Shake well before using.

Keep TRILEPTAL and all medicines out of the reach of children.

General Information about the safe and effective use of TRILEPTAL

Medicines are sometimes prescribed for purposes other than those listed in a Medication Guide. Do not use TRILEPTAL for a condition for which it was not prescribed. Do not give TRILEPTAL to other people, even if they have the same symptoms that you have. It may harm them.

This Medication Guide summarizes the most important information about TRILEPTAL. If you would like more information, talk with your healthcare provider. You can ask your pharmacist or healthcare provider for the full prescribing information about TRILEPTAL that is written for health professionals.

For more information, go to www.pharma.us.novartis.com or call 1-888-669-6682.

What are the ingredients in TRILEPTAL?

Active ingredient: oxcarbazepine

Inactive ingredients:

- Tablets: colloidal silicon dioxide, crospovidone, hydroxypropyl methylcellulose, iron oxide, magnesium stearate, microcrystalline cellulose, polyethylene glycol, talc and titanium dioxide.
- Oral suspension: ascorbic acid, dispersible cellulose, ethanol, macrogol stearate, methyl parahydroxybenzoate, propylene glycol, propyl parahydroxybenzoate, purified water, sodium saccharin, sorbic acid, sorbitol, yellow-plum-lemon aroma.

This Medication Guide has been approved by the U.S. Food and Drug Administration.

Distributed by:

Novartis Pharmaceuticals Corporation

East Hanover, New Jersey 07936

T2011-25/T2011-26

March 2011/March 2011

© Novartis

Relabeling and Repackaging by:
Physicians Total Care, Inc.
Tulsa, Oklahoma 74146

PACKAGE LABEL

PRINCIPAL DISPLAY PANEL

Package Label – 150 mg

Rx Only

Trileptal® (oxcarbazepine)

PHARMACIST: DISPENSE WITH MEDICATION
GUIDE ATTACHED OR PROVIDED SEPARATELY.

PACKAGE LABEL

PRINCIPAL DISPLAY PANEL

Package Label – 300 mg

Rx Only

Trileptal® (oxcarbazepine)

PHARMACIST: DISPENSE WITH MEDICATION
GUIDE ATTACHED OR PROVIDED SEPARATELY.